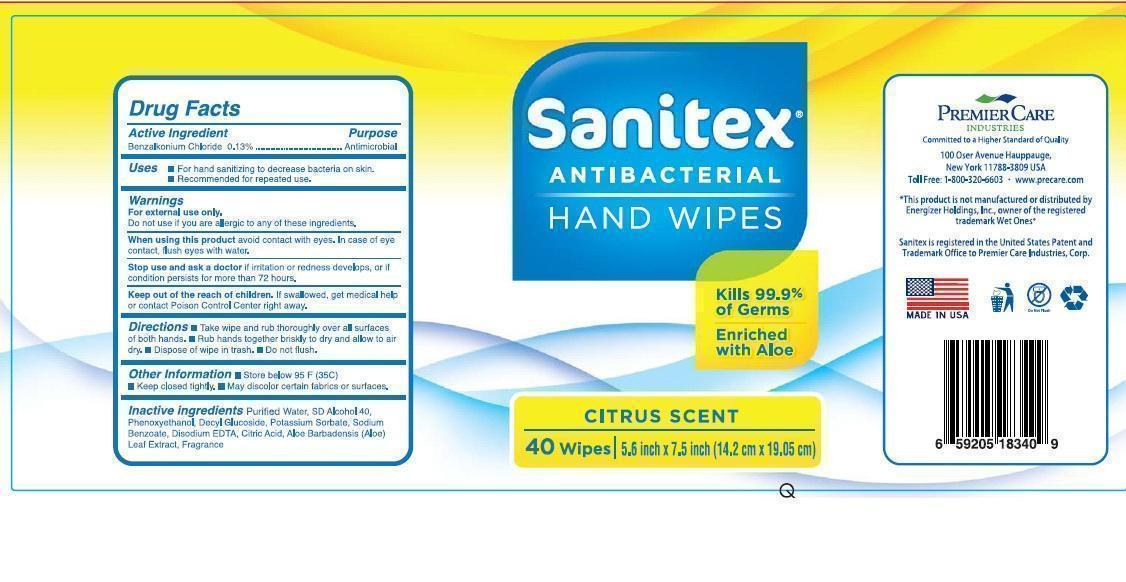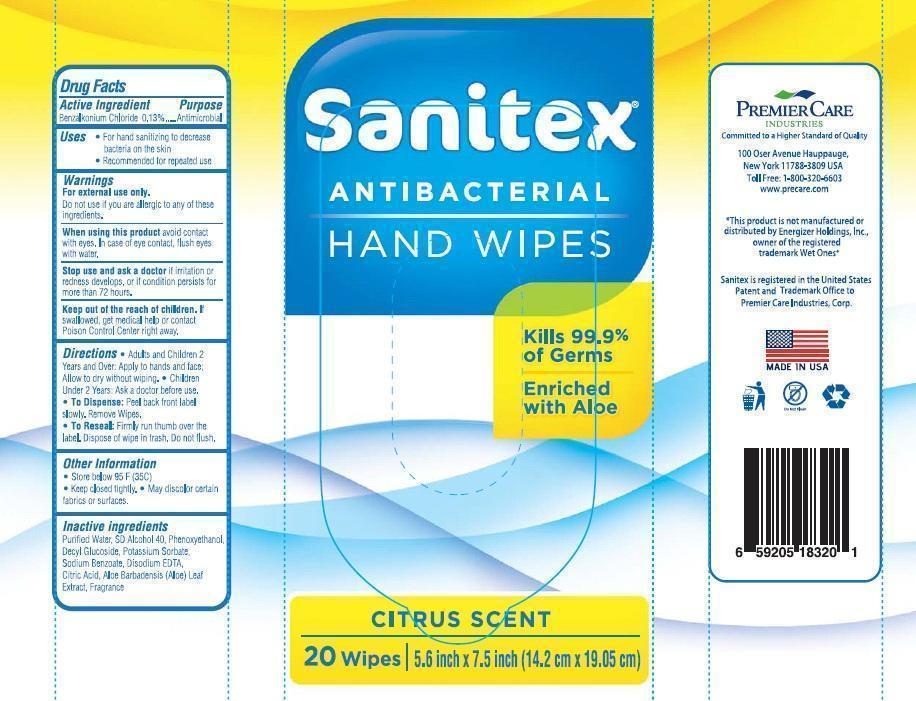 DRUG LABEL: Sanitex Antibacterial Hand Wipes
NDC: 53118-001 | Form: SWAB
Manufacturer: PREMIER CARE INDUSTRIES, INC
Category: otc | Type: HUMAN OTC DRUG LABEL
Date: 20150618

ACTIVE INGREDIENTS: BENZALKONIUM CHLORIDE 0.26 g/100 g
INACTIVE INGREDIENTS: WATER; ALCOHOL ; PHENOXYETHANOL; DECYL GLUCOSIDE; POTASSIUM SORBATE; SODIUM BENZOATE; EDETATE DISODIUM; CITRIC ACID MONOHYDRATE; ALOE VERA LEAF

Drug Facts

Active Ingredient

Benzalkonium Chloride 0.13%

Purpose

Antimicrobial

Uses

- For hand sanitizing to decrease bacteria on skin.
- Recommended for repeated use.

Warnings

For external use only.

Do not use if

you are allergic to any of these ingredients.

When using this product

avoid contact with eyes. In case of eye contact, flush eyes with water.

Stop use and ask a doctor

if irritation or redness develops, or if condition persists for more than 72 hours.

Keep out of the reach children.

If swallowed, get medical help or contact Poison Control Center right away.

Directions

For 40 Count wipes:

- Take wipe and rub thoroughly over all surfaces of both hands.
- Rub hands together briskly to dry and allow to air dry.
- Dispose of wipe in trash.
- Do not flush.

For 20 Count wipes:

Adults and Children 2 Years and Over: Apply to hands and face. Allow to dry without wiping.

Children Under 2 Years: Ask a doctor before use.

- To Dispense:Peel back front label slowly. Remove Wipes.

- To Reseal: Firmly run thumb over the label. Dispose of wipe in trash. Do not flush.

Other Information

- Store below 95 F (35 C)
- Keep closed tightly.
- May discolor certain fabrics or surfaces.

Inactive ingredients

Purified Water, SD Alcohol 40, Phenoxyethanol, Decyl Glucoside, Potassium Sorbate, Sodium Benzoate, Disodium EDTA, Citric Acid, Aloe Barbadensis (Aloe) Leaf Extract, Fragrance

Principal Display Panel

Sanitex®

Antibacterial

HAND WIPES

Kills 99.9% of Germs

Enriched with Aloe

CITRUS SCENT

40 wipes| 5.6 inch x 7.5 inch (14.2 cm x 19.05 cm)

Sanitex®

Antibacterial

HAND WIPES

Kills 99.9% of Germs

Enriched with Aloe

CITRUS SCENT

20 wipes| 5.6 inch x 7.5 inch (14.2 cm x 19.05 cm)